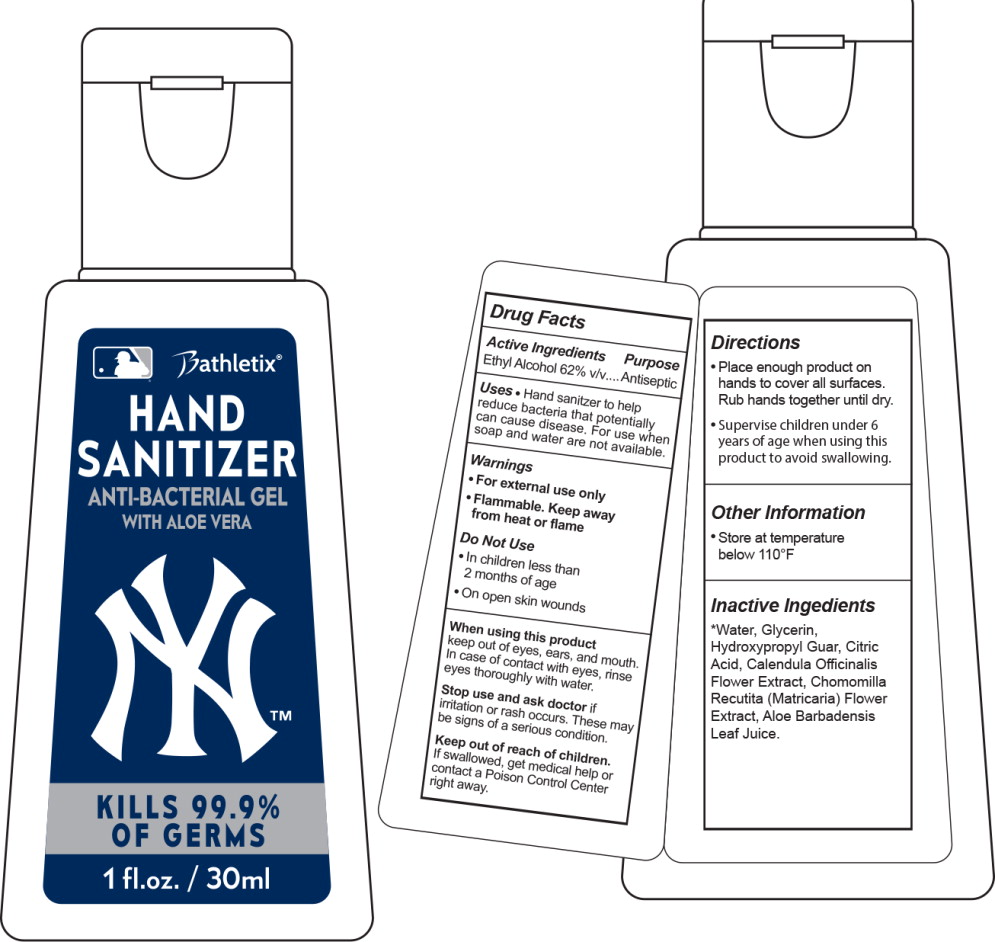 DRUG LABEL: Handsanitizer 
NDC: 90108-050 | Form: LIQUID
Manufacturer: Bathletix
Category: otc | Type: HUMAN OTC DRUG LABEL
Date: 20200824

ACTIVE INGREDIENTS: Alcohol 75 ug/1 1
INACTIVE INGREDIENTS: Water; Glycerin; GUARAPROLOSE (1300 MPA.S AT 1%); Aloe Vera Leaf; Citric Acid Monohydrate; Calendula Officinalis Flower; Matricaria Chamomilla Whole

Drug Facts

Active Ingredients

Ethyl Alcohol 62% v/v

Purpose

Antiseptic

Uses

- Hand sanitzer to help reduce bacteria that potentially can cause disease. For use when soap and water are not available.

Warnings

- For external use only
- Flammable. Keep away from heat or flame

Do Not Use

- In children less than 2 months of age
- On open skin wounds

When using this product

keep out of eyes, ears, and mouth. In case of contact with eyes, rinse eyes thoroughly with water.

Stop use and ask doctor if irritation or rash occurs. These may be signs of a serious condition.

Keep out of reach of children.

If swallowed, get medical help or contact a Poison Control Center right away.

Directions

- Place enough product on hands to cover all surfaces. Rub hands together until dry.
- Supervise children under 6 years of age when using this product to avoid swallowing.

Other Information

- Store at temperature below 110°F

Inactive Ingredients

*Water, Glycerin, Hydroxypropyl Guar, Citric Acid, Calendula Officinalis Flower Extract, Chomomilla Recutita (Matricaria) Flower Extract, Aloe Barbadensis Leaf Juice.

Principal Display Panel – 30 mL Bottle Label

Bathletix®
HAND
SANITIZER

ANTI-BACTERIAL GEL
WITH ALOE VERA

KILLS 99.9%
OF GERMS

1 fl.oz./30ml